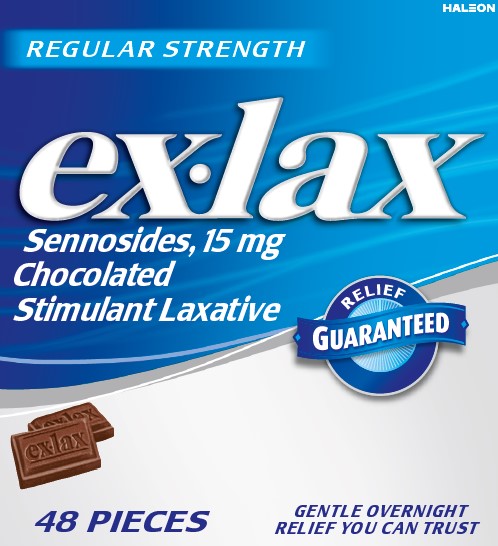 DRUG LABEL: EX-LAX
NDC: 0067-8140 | Form: TABLET, CHEWABLE
Manufacturer: Haleon US Holdings LLC
Category: otc | Type: HUMAN OTC DRUG LABEL
Date: 20241217

ACTIVE INGREDIENTS: SENNOSIDES 15 mg/1 1
INACTIVE INGREDIENTS: COCOA; HYDROGENATED PALM KERNEL OIL; SOYBEAN LECITHIN; SUCROSE; VANILLIN; SODIUM CHLORIDE; WHEY

Drug Facts

Active ingredient (in each piece)

Sennosides 15 mg

Purpose

Stimulant laxative

Uses

- relieves occasional constipation (irregularity)
- generally produces bowel movement in 6 to 12 hours

Warnings

Do not use

laxative products when abdominal pain, nausea or vomiting are present unless directed by a doctor

Ask a doctor before use if you have

noticed a sudden change in bowel habits that persists over a period of 2 weeks

Ask a doctor or pharmacist before use if you are

taking any other drug. Laxatives may affect how other drugs work. Take this product 2 or more hours before or after other drugs.

When using this product

do not use for a period longer than 1 week

Stop use and ask a doctor if

rectal bleeding or failure to have a bowel movement occur after use of a laxative. These may be signs of a serious condition.

If pregnant or breast-feeding,

ask a health professional before use.

Keep out of reach of children.

In case of overdose, get medical help or contact a Poison Control Center right away.

Directions

adults and children 12 years of age and older | chew 2 chocolated pieces once or twice daily
children 6 to under 12 years of age | chew 1 chocolated piece once or twice daily
children under 6 years of age | ask a doctor

Other information

- each piece contains: potassium 10 mg
- store at 15-25oC (59-77oF)

Inactive ingredients

cocoa powder, hydrogenated vegetable oils (palm kernel, palm), salt, soy lecithin, sugar, vanilla, whey powder (milk)

Questions or comments?

call 1-855-221-5432

Generic Section

Tamper Evident Feature: Do not use if carton or inner foil wrapping is damaged or open.

The Ex-Lax Guarantee: When taken as directed, Ex-Lax is guaranteed to work gently and effectively overnight or your money back. Return product to Haleon, attention Consumer Affairs, for full refund.

Principal Display Panel

REGULAR STRENGTH

ex-lax

Sennosides, 15 mg

Chocolated Stimulant Laxative

Relief Guaranteed

48 PIECES

GENTLE OVERNIGHT RELIEF YOU CAN TRUST